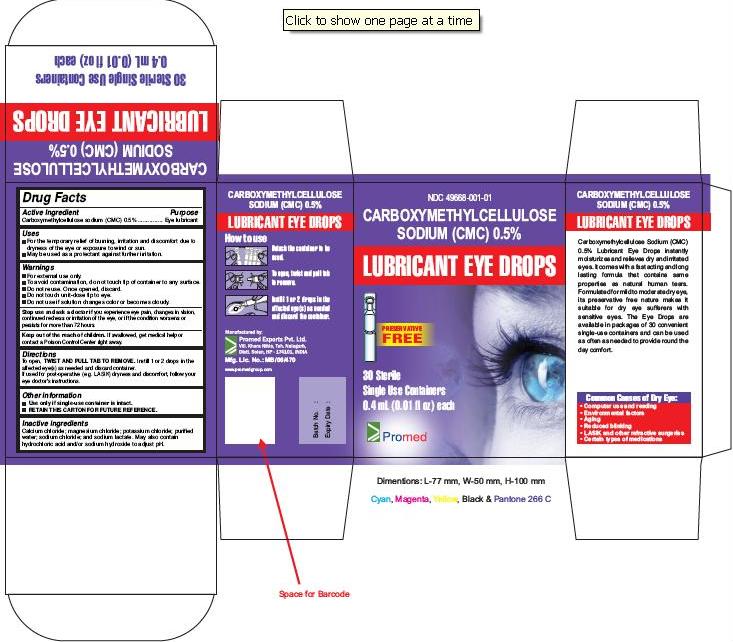 DRUG LABEL: Carboxymethylcellulose sodium
NDC: 49668-001 | Form: SOLUTION
Manufacturer: PROMED EXPORTS PRIVATE LIMITED
Category: otc | Type: Human OTC Drug Label
Date: 20090827

ACTIVE INGREDIENTS: CARBOXYMETHYLCELLULOSE SODIUM 5 mg/1 mL
INACTIVE INGREDIENTS: CALCIUM CHLORIDE; MAGNESIUM CHLORIDE; POTASSIUM CHLORIDE; WATER; SODIUM CHLORIDE; SODIUM LACTATE; HYDROCHLORIC ACID; SODIUM HYDROXIDE

ACTIVE INGREDIENT

Carboxymethylcellulose sodium (CMC) 0.5% ............... Eye lubricant

USES

- For the temporary relief of burning, irritation and discomfort due to dryness of the eye or exposure to wind or sun.
- May be used as a protectant against further irritation.

WARNINGS

- For external use only.
- To avoid contamination, do not touch tip of container to any surface. Do not reuse. Once opened, discard.
- Do not touch unit-dose tip to eye.
- Do not use if solution changes color or becomes cloudy.

STOP USE AND ASK A DOCTOR

If you experience eye pain, changes in vision, continued redness or irritation of the eye, or if the condition worsens or persists for more than 72 hours.

KEEP OUT OF REACH OF CHILDREN

If swallowed, get medical help or contact a Poison Control Center right away.

DIRECTIONS

To open, TWIST AND PULL TAB TO REMOVE. Instill 1 or 2 drops in the affected eye(s) as needed and discard container.

If used for post-operative (e.g. LASIK) dryness and discomfort, follow your eye doctor’s instructions.

OTHER INFORMATION

- Use only if single-use container is intact.
- RETAIN THIS CARTON FOR FUTURE REFERENCE.

INACTIVE INGREDIENTS

Calcium chloride; magnesium chloride; potassium chloride; purified water; sodium chloride; and sodium lactate. May also contain hydrochloric acid and/or sodium hydroxide to adjust pH.

PACKAGE LABEL.PRINCIPAL DISPLAY PANEL- 30 Sterile Single Use Containers

CARBOXYMETHYLCELLULOSE SODIUM (CMC) 0.5%
LUBRICANT EYE DROPS